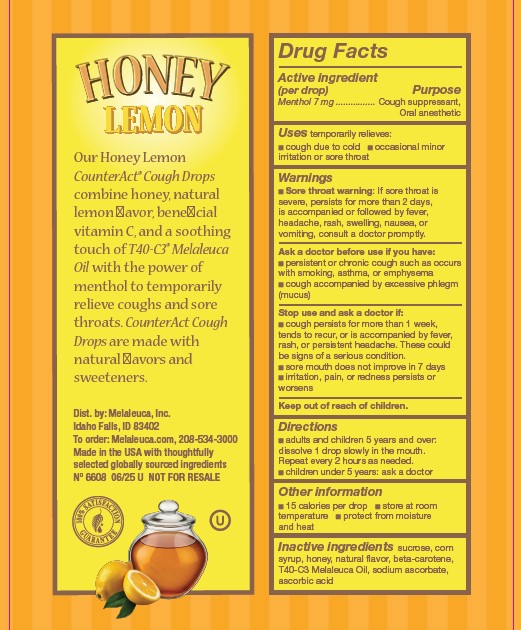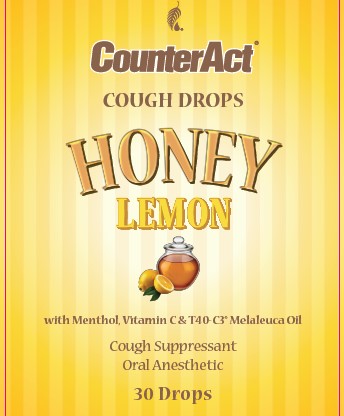 DRUG LABEL: CounterAct
NDC: 54473-132 | Form: LOZENGE
Manufacturer: Melaleuca, Inc.
Category: otc | Type: HUMAN OTC DRUG LABEL
Date: 20250228

ACTIVE INGREDIENTS: MENTHOL 7 mg/1 1
INACTIVE INGREDIENTS: ASCORBIC ACID; .BETA.-CAROTENE; CORN SYRUP; HONEY; SODIUM ASCORBATE; SUCROSE; TEA TREE OIL

CounterAct Cough Drops Honey Lemon Content of Label

Active ingredient (in each drop)
Menthol 7 mg

Purpose
Cough suppressant, oral anesthetic

INDICATIONS AND USAGE

Uses temporarily relieves:
■ cough associated with a cold
■ occasional minor irritation or sore throat

Warnings

■ Sore throat warning: If sore throat is severe, persists for more than 2 days, is accompanied or followed by fever, headache, rash, swelling, nausea, or vomiting, consult a doctor promptly.

Ask a doctor before use if you have:
■ persistent or chronic cough such as occurs with smoking, asthma, or emphysema
■ cough accompanied by excessive phlegm (mucus)

Stop use and ask a doctor if:
■ cough persists for more than 1 week, tends to recur, or is accompanied by fever, rash, or persistent headache. These could be signs of a serious condition.
■ sore mouth does not improve in 7 days
■ irritation, pain, or redness persists or worsens

Keep out of reach of children.

Directions
■ adults and children 5 years and over: dissolve 1 drop slowly in the mouth.
Repeat every 2 hours as needed.
■ children under 5 years: ask a doctor

Other information

- 15 calories per lozenge
- store at room temperature
- protect from moisture and heat

Inactive ingredients

sucrose, corn syrup, honey, natural flavor, beta-carotene, T40-C3 Melaleuca oil, sodium ascorbate, ascorbic acid

RECENT MAJOR CHANGES

Indications and Usage section verbiage slightly changed FROM:
■ cough associated with a cold or inhaled ingredients ■ occasional minor irritation, pain, sore mouth, and sore throat
TO:
■ cough due to cold ■ occasional minor irritation or sore throat"

Dosage and Administration section changed FROM:
adults and children 5 years and over: dissolve 1 drop slowly in the mouth. May be repeated every hour as needed or as directed by a doctor.
children under 5 years: ask a doctor
TO:
■ adults and children 5 years and over: dissolve 1 drop slowly in the mouth.
Repeat every 2 hours as needed.
■ children under 5 years: ask a doctor